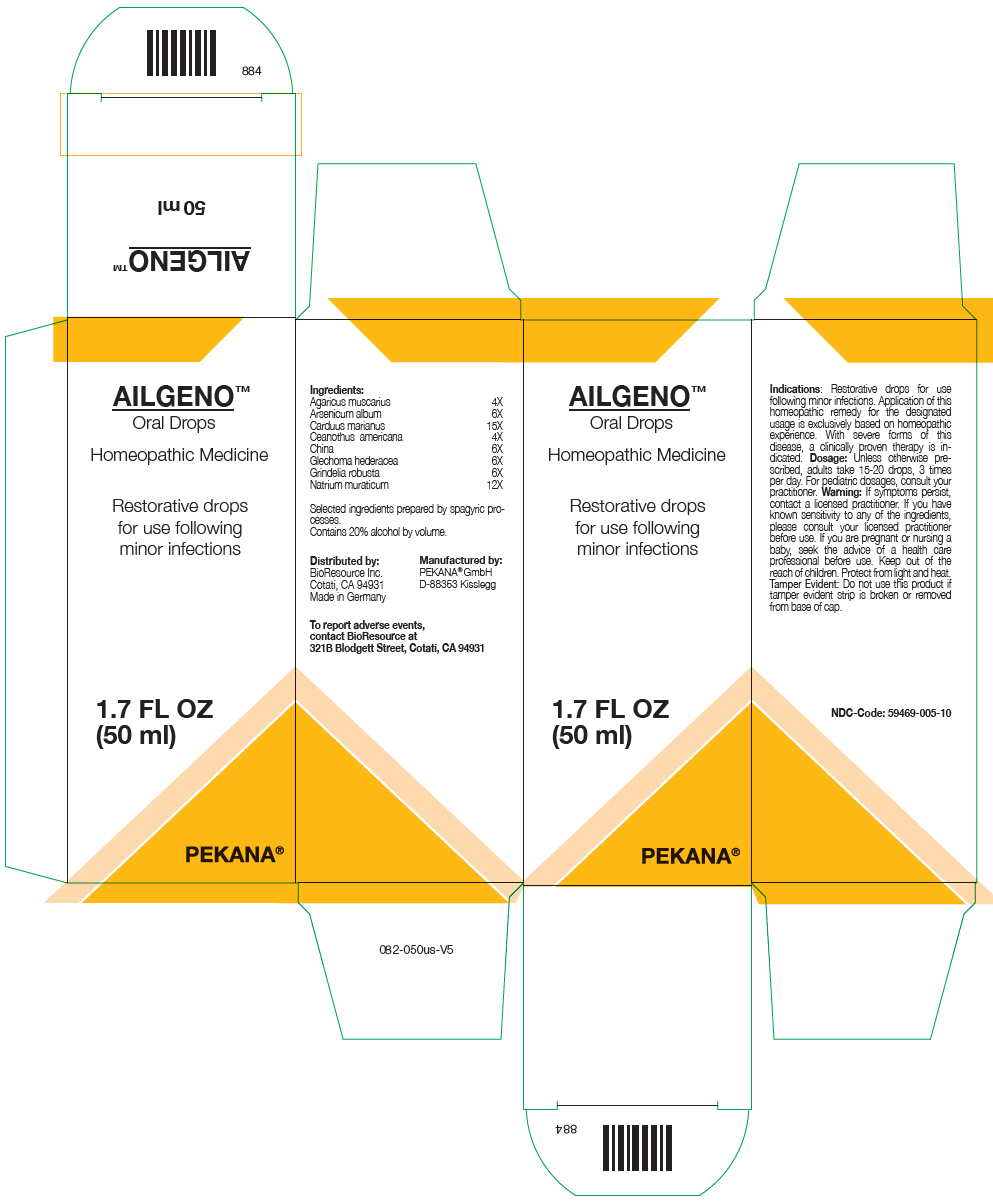 DRUG LABEL: AILGENO
NDC: 59469-005 | Form: SOLUTION/ DROPS
Manufacturer: PEKANA Naturheilmittel GmbH
Category: homeopathic | Type: HUMAN OTC DRUG LABEL
Date: 20221221

ACTIVE INGREDIENTS: Amanita muscaria Fruiting Body 4 [hp_X]/50 mL; Arsenic trioxide 6 [hp_X]/50 mL; Milk Thistle 15 [hp_X]/50 mL; Ceanothus americanus Leaf 4 [hp_X]/50 mL; Cinchona officinalis Bark 6 [hp_X]/50 mL; Glechoma hederacea Flowering Top 6 [hp_X]/50 mL; Grindelia hirsutula whole 6 [hp_X]/50 mL; Sodium chloride 12 [hp_X]/50 mL
INACTIVE INGREDIENTS: Water; Alcohol

AILGENO™

ACTIVE INGREDIENT

Ingredients:
Agaricus muscarius | 4X
Arsenicum album | 6X
Carduus marianus | 15X
Ceanothus americana | 4X
China | 6X
Glechoma hederacea | 6X
Grindelia robusta | 6X
Natrium muraticum | 12X

Selected ingredients prepared by spagyric processes.

INACTIVE INGREDIENT

Contains 20% alcohol by volume.

Indications

PURPOSE

Restorative drops for use following minor infections. Application of this homeopathic remedy for the designated usage is exclusively based on homeopathic experience. With severe forms of this disease, a clinically proven therapy is indicated.

Dosage

Unless otherwise prescribed, adults take 15-20 drops, 3 times per day. For pediatric dosages, consult your practitioner.

Warning

ASK DOCTOR

If symptoms persist, contact a licensed practitioner. If you have known sensitivity to any of the ingredients, please consult your licensed practitioner before use. If you are pregnant or nursing a baby, seek the advice of a health care professional before use.

Keep out of the reach of children.

STORAGE AND HANDLING

Protect from light and heat.

Tamper Evident

Do not use this product if tamper evident strip is broken or removed from base of cap.

QUESTIONS

To report adverse events, contact BioResource at 321B Blodgett Street, Cotati, CA 94931

Distributed by:
BioResource Inc.
Cotati, CA 94931

Manufactured by:
PEKANA® GmbH
D-88353 Kisslegg

PRINCIPAL DISPLAY PANEL - 50 ml Bottle Box

AILGENO™
Oral Drops

Homeopathic Medicine

Restorative drops
for use following
minor infections

1.7 FL OZ
(50 ml)

PEKANA®